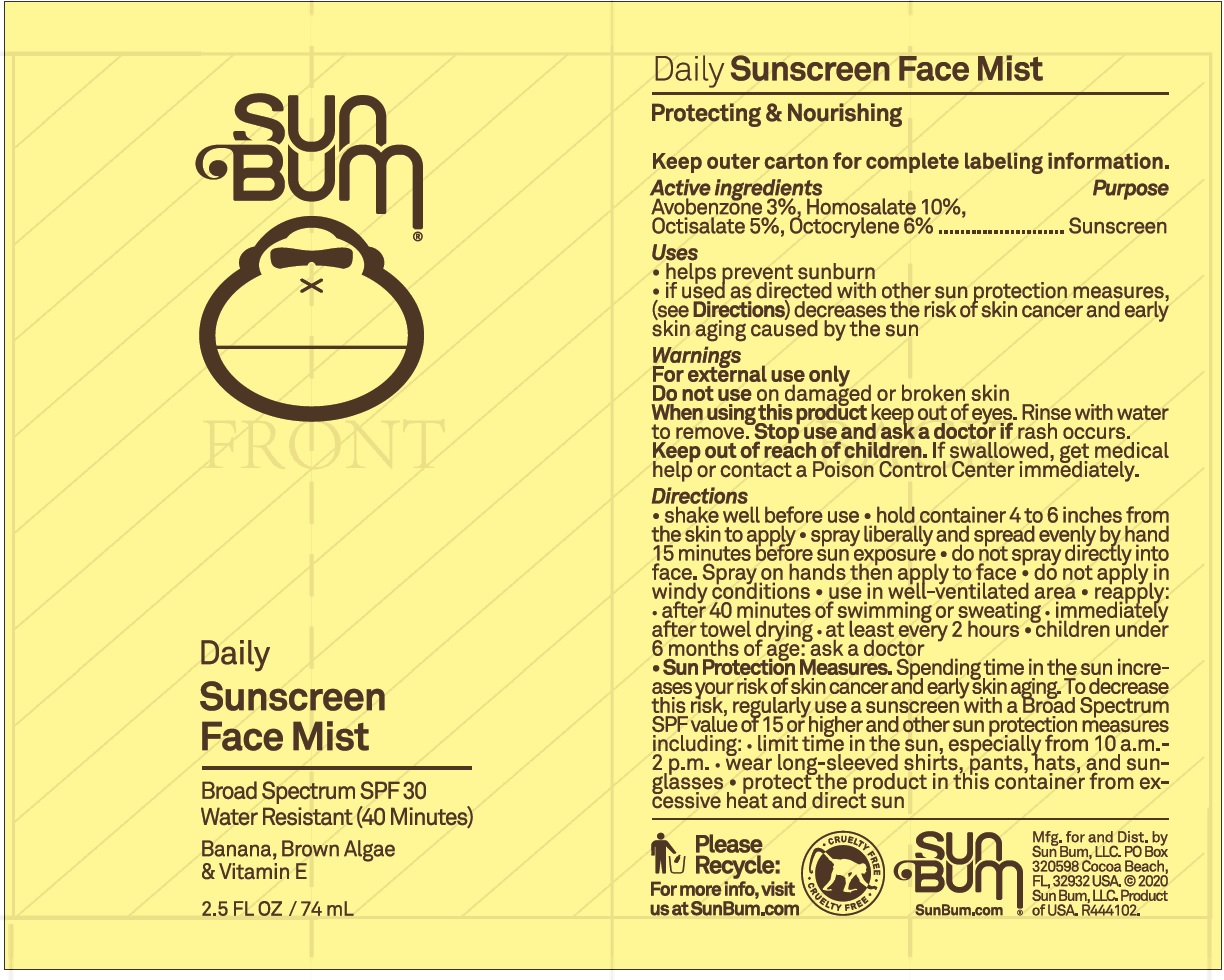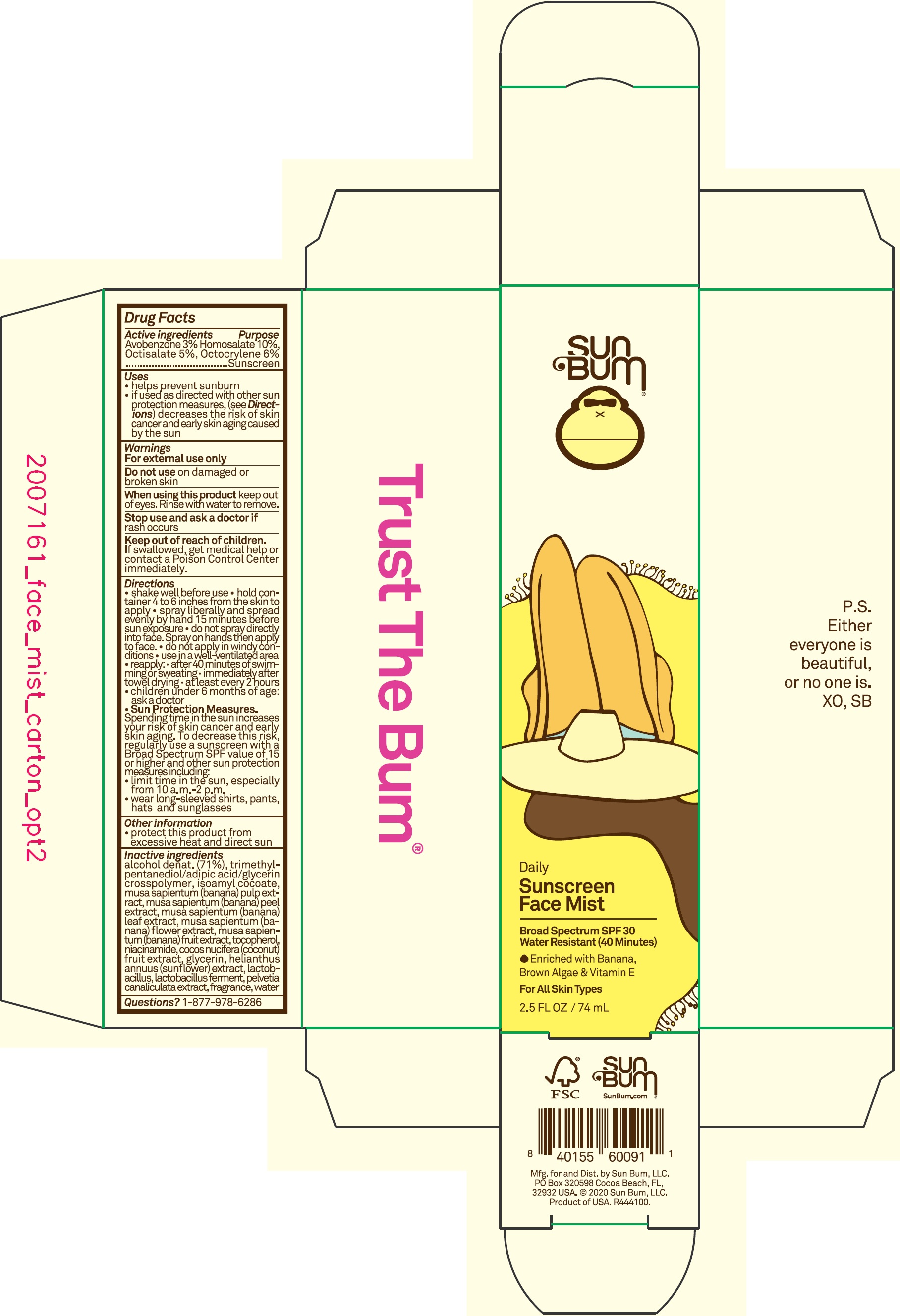 DRUG LABEL: Sun Bum Daily Sunscreen Face Mist SPF30
NDC: 69039-636 | Form: LOTION
Manufacturer: Sun Bum LLC
Category: otc | Type: HUMAN OTC DRUG LABEL
Date: 20220204

ACTIVE INGREDIENTS: AVOBENZONE 30 mg/1 mL; HOMOSALATE 100 mg/1 mL; OCTISALATE 50 mg/1 mL; OCTOCRYLENE 60 mg/1 mL
INACTIVE INGREDIENTS: ALCOHOL; TRIMETHYLPENTANEDIOL/ADIPIC ACID/GLYCERIN CROSSPOLYMER (25000 MPA.S); ISOAMYL COCOATE; CETOSTEARYL ALCOHOL; CAPRYLOYL GLYCERIN/SEBACIC ACID COPOLYMER (2000 MPA.S); HYDRATED SILICA; BANANA PEEL; MUSA X PARADISIACA LEAF; MUSA X PARADISIACA FLOWER; BANANA; TOCOPHEROL; NIACINAMIDE; COCONUT; GLYCERIN; HELIANTHUS ANNUUS FLOWERING TOP; PELVETIA CANALICULATA; WATER

Sun Bum Daily Sunscreen Face Mist SPF30

Active ingredients

Avobenzone 3%,

Homosalate 10%,

Octisalate 5%,

Octocrylene 6%

Purpose

Sunscreen

Uses

- helps prevent sunburn
- if used as directed with other sun protection measures, (see Directions) decreases the risk of skin cancer and early skin aging caused by the sun

Warnings

For external use only

Do not use

on damaged or broken skin

When using this product

keep out of eyes. Rinse with water to remove.

Stop use and ask a doctor if

rash occurs

Keep out of reach of children.

If swallowed, get medical help or contact a Poison Control Center immediately.

Directions

- shake well before use
- hold container 4 to 6 inches from the skin to apply
- spray liberally and spread evenly by hand 15 minutes before sun exposure
- do not spray directly into face.
- do not apply in windy conditions
- use in a well-ventilated area
- reapply: • after 40 minutes of swimming or sweating • immediately after towel drying • at least every 2 hours
- children under 6 months of age: ask a doctor

Sun Protection Measures. Spending time in the sun increases your risk of skin cancer and early skin aging. To decrease this risk, regularly use a sunscreen with a Broad Spectrum SPF value of 15 or higher and other sun protection measures including:

- limit time in the sun, especially from 10 a.m.-2 p.m.
- wear long-sleeved shirts, pants, hats and sunglasses

Other information

protect this product from excessive heat and direct sun

Inactive ingredients

alcohol denat. (71%), trimethyl pentanediol/adipic acid/glycerin crosspolymer, isoamyl cocoate, musa sapientum (banana) pulp extract, musa sapientum (banana) peel extract, musa sapientum (banana) leaf extract, musa sapientum (banana) flower extract, musa sapientum (banana) fruit extract, tocopherol, niacinamide, cocos nucifera (coconut) fruit extract, glycerin, helianthus annuus (sunflower) extract, lactobacillus, lactobacillus ferment, pelvetia canaliculata extract, fragrance, water

Questions?

1-877-978-6286